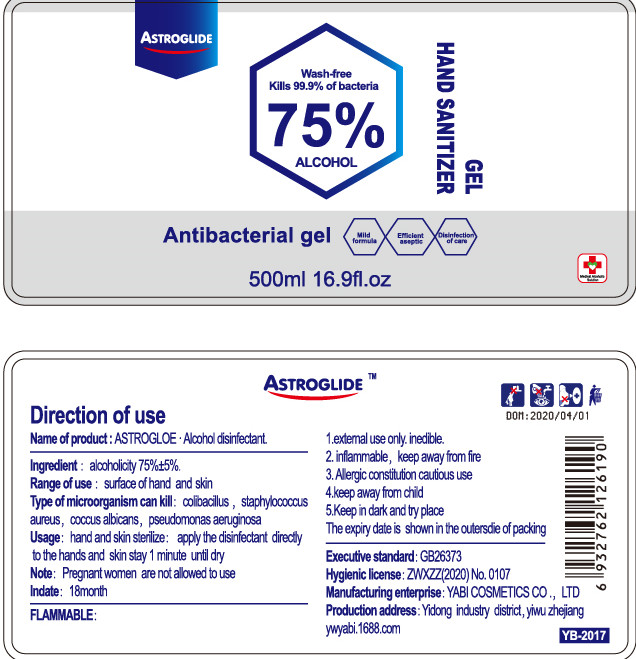 DRUG LABEL: Hand sanitizer gel
NDC: 52955-001 | Form: GEL
Manufacturer: Yiwu Yabi Cosmetics Co.,Ltd.
Category: otc | Type: HUMAN OTC DRUG LABEL
Date: 20200428

ACTIVE INGREDIENTS: ALCOHOL 375 mL/500 mL
INACTIVE INGREDIENTS: GLYCERIN; TROLAMINE; WATER; CARBOMER COPOLYMER TYPE A (ALLYL PENTAERYTHRITOL CROSSLINKED)

DOSAGE AND ADMINISTRATION

inflammable, keep away from fire.

INACTIVE INGREDIENT

AQUA

GLYCERIN

TRIETHANOLAMINE

CARBOMER

INDICATIONS AND USAGE

apply the disinfectant directly the hands and skin stay 1minute until dry.

ACTIVE INGREDIENT

ALCOHOL

keep out of reach of children

PURPOSE

Disinfection
Sterilization
No Rinseing

WARNINGS

1.extemal use only. inedible
2.inflammable, keep away from fire.
3.Allergic constitution cautious use
4.keep away from child
5.Keep in dark and try place